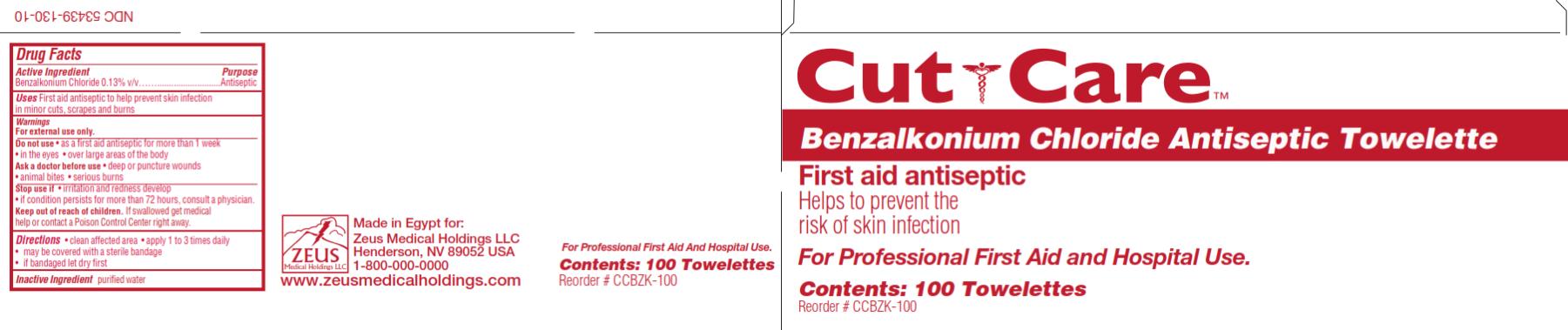 DRUG LABEL: Cut Care Benzalkonium Chloride Antiseptic
NDC: 53439-130 | Form: SWAB
Manufacturer: Zeus Medical Holdings LLC
Category: otc | Type: HUMAN OTC DRUG LABEL
Date: 20130909

ACTIVE INGREDIENTS: BENZALKONIUM CHLORIDE 1.3 mg/1 1
INACTIVE INGREDIENTS: WATER

Cut Care Benzalkonium Chloride Antiseptic Towlette

Active Ingredient

Benzalkonium Chloride 0.13% v/v

Purpose

Antiseptic

Uses

First aid antiseptic to help prevent skin infection in minor cuts, scrapes and burns

Warnings

For external use only.

Do not use

- as a first aid antiseptic for more than 1 week
- in the eyes
- over large areas of the body

Ask a doctor before use

- deep or puncture wounds
- animal bites
- serious burns

Stop use if

- irritation and redness develop
- if condition persists for more than 72 hours, consult a physician.

Keep out of reach of children

If swallowed get medical help or contact a Poison Control Center right away.

Directions

- clean affected area
- apply 1 to 3 times daily
- may be covered with a sterile bandage
- if bandaged let dry first

Inactive ingredient

purified water

PRINCIPAL DISPLAY PANEL

NDC 53439-130-10
Cut Care
Benzalkonium Chloride Antiseptic Towelette
First aid antiseptic
Contents: 100 Towelettes